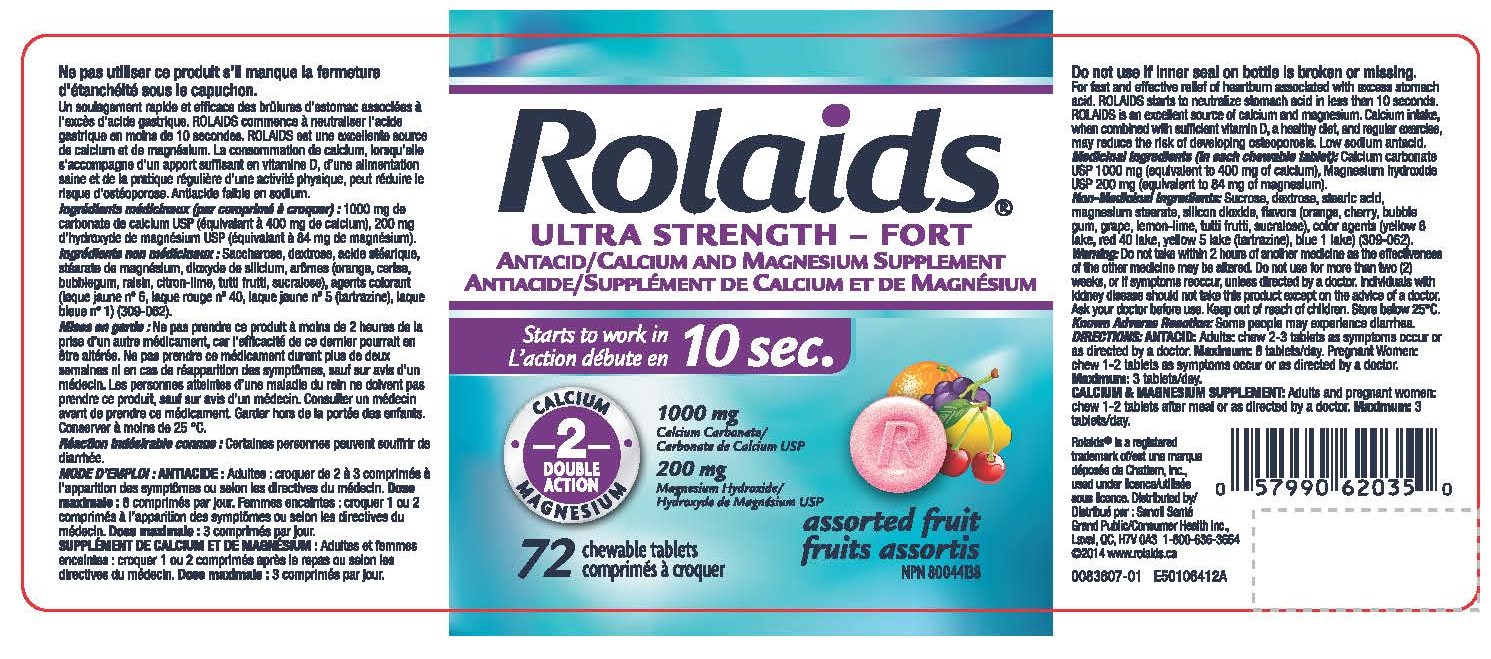 DRUG LABEL: Calcium Carbonate, Magnesium Hydroxide
NDC: 10267-0019 | Form: TABLET, CHEWABLE
Manufacturer: Contract Pharmacal Corp.
Category: otc | Type: HUMAN OTC DRUG LABEL
Date: 20200407

ACTIVE INGREDIENTS: MAGNESIUM HYDROXIDE 200 mg/1 1; CALCIUM CARBONATE 1000 mg/1 1
INACTIVE INGREDIENTS: FD&C YELLOW NO. 6; ORANGE; GRAPE; SUCROSE; FD&C RED NO. 40; SILICON DIOXIDE; LEMON; DEXTROSE; FD&C BLUE NO. 1; MALTODEXTRIN; FD&C YELLOW NO. 5; CHERRY; MAGNESIUM STEARATE; SUCRALOSE; STEARIC ACID

4444- Export